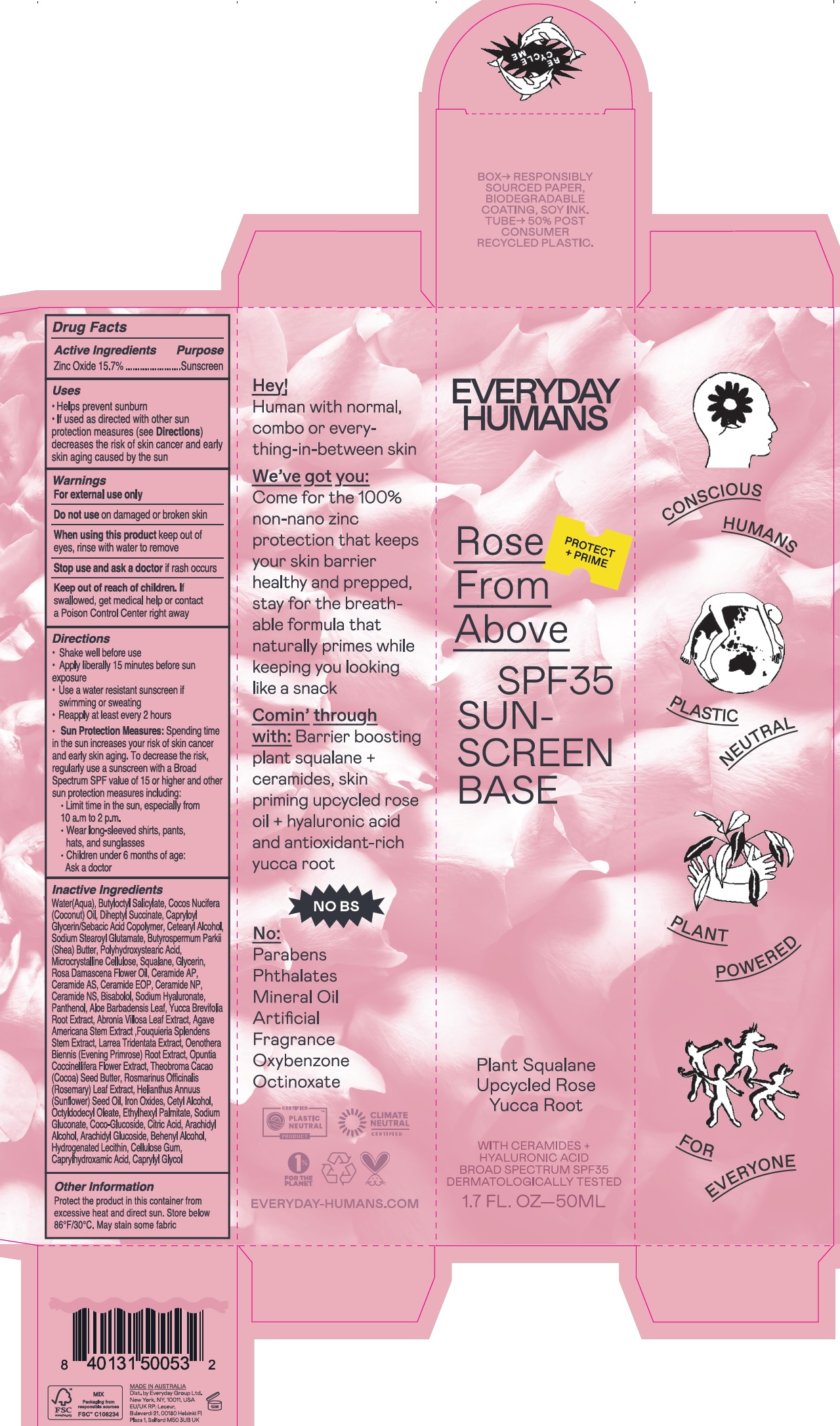 DRUG LABEL: Everydayhumans Rose from above SPF 35 sunscreen base
NDC: 72098-006 | Form: LOTION
Manufacturer: EVERYDAY GROUP LIMITED
Category: otc | Type: HUMAN OTC DRUG LABEL
Date: 20231215

ACTIVE INGREDIENTS: ZINC OXIDE 157 mg/1 mL
INACTIVE INGREDIENTS: WATER; BUTYLOCTYL SALICYLATE; COCONUT OIL; DIHEPTYL SUCCINATE; CETOSTEARYL ALCOHOL; SODIUM STEAROYL GLUTAMATE; SHEA BUTTER; MICROCRYSTALLINE CELLULOSE; SQUALANE; GLYCERIN; ROSA X DAMASCENA FLOWER OIL; CERAMIDE AP; CERAMIDE NP; CERAMIDE NG; LEVOMENOL; HYALURONATE SODIUM; PANTHENOL; ALOE VERA LEAF; YUCCA BREVIFOLIA ROOT; ABRONIA VILLOSA LEAF; AGAVE AMERICANA STEM; FOUQUIERIA SPLENDENS STEM; OENOTHERA BIENNIS ROOT; OPUNTIA COCHENILLIFERA FLOWER; COCOA BUTTER; ROSEMARY; SUNFLOWER OIL; FERRIC OXIDE RED; CETYL ALCOHOL; OCTYLDODECYL OLEATE; ETHYLHEXYL PALMITATE; SODIUM GLUCONATE; COCO GLUCOSIDE; CITRIC ACID MONOHYDRATE; ARACHIDYL ALCOHOL; ARACHIDYL GLUCOSIDE; DOCOSANOL; CARBOXYMETHYLCELLULOSE SODIUM, UNSPECIFIED; CAPRYLHYDROXAMIC ACID; CAPRYLYL GLYCOL

Everydayhumans Rose from above SPF 35 sunscreen base

Active Ingredients

Zinc Oxide 15.7%

Purpose

Sunscreen

Uses

- Helps prevent sunburn
- If used as directed with other sun protection measures (see) decreases the risk of skin cancer and early skin aging caused by the sun Directions

Warnings

For external use only

Do not use

on damaged or broken skin

When using this product

keep out of eyes, rinse with water to remove

Stop use and ask a doctor

ir rash occurs

Keep out of reach of children.

If swallowed, get medical help or contact a Poison Control Center right away

Directions

- Shake well before use
- Apply liberally 15 minutes before sun exposure
- Use a water resistant sunscreen if swimming or sweating
- Reapply at least every 2 hours
- Spending time in the sun increases your risk of skin cancer and early skin aging. To decrease the risk, regularly use a sunscreen with a Broad Spectrum SPF value of 15 or higher and other sun protection measures including: Sun Protection Measures:
- Limit time in the sun, especially from 10 a.m to 2 p.m.
- Wear long-sleeved shirts, pants, hats, and sunglasses
- Children under 6 months of age: Ask a doctor

Inactive Ingredients

Water(Aqua), Butyloctyl Salicylate, Cocos Nucifera (Coconut) Oil, Diheptyl Succinate, Capryloyl Glycerin/Sebacic Acid Copolymer, Cetearyl Alcohol, Sodium Stearoyl Glutamate, Butyrospermum Parkii (Shea) Butter, Polyhydroxystearic Acid, Microcrystalline Cellulose, Squalane, Glycerin, Rosa Damascena Flower Oil, Ceramide AP, Ceramide AS, Ceramide EOP, Ceramide NP, Ceramide NS, Bisabolol, Sodium Hyaluronate, Panthenol, Aloe Barbadensis Leaf, Yucca Brevifolia Root Extract, Abronia Villosa Leaf Extract, Agave Americana Stem Extract, Fouquieria Splendens Stem Extract, Larrea Tridentata Extract, Oenothera Biennis (Evening Primrose) Root Extract, Opuntia Coccinellifera Flower Extract, Theobroma Cacao (Cocoa) Seed Butter, Rosmarinus Officinalis (Rosemary) Leaf Extract, Helianthus Annuus (Sunflower) Seed Oil, Iron Oxides, Cetyl Alcohol, Octyldodecyl Oleate, Ethylhexyl Palmitate, Sodium Gluconate, Coco-Glucoside, Citric Acid, Arachidyl Alcohol, Arachidyl Glucoside, Behenyl Alcohol, Hydrogenated Lecithin, Cellulose Gum, Caprylhydroxamic Acid, Caprylyl Glycol

Other Information

Protect the product in this container from excessive heat and direct sun. Store below 86°F/30°C. May stain some fabric